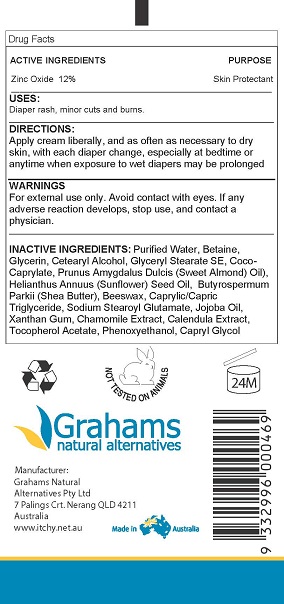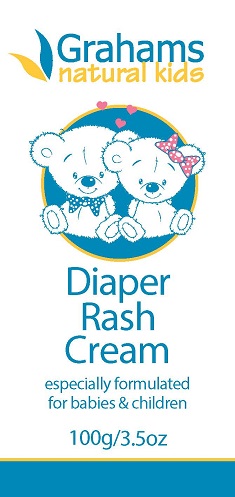 DRUG LABEL: Grahams Natural Diaper Rash
NDC: 42387-135 | Form: CREAM
Manufacturer: Grahams Natural Alternatives Pty Ltd
Category: otc | Type: HUMAN OTC DRUG LABEL
Date: 20160830

ACTIVE INGREDIENTS: ZINC OXIDE 12 g/100 g
INACTIVE INGREDIENTS: JOJOBA OIL; CHAMOMILE; POTASSIUM SORBATE; MEDIUM-CHAIN TRIGLYCERIDES; WATER; YELLOW WAX; GLYCERIN; CETOSTEARYL ALCOHOL; SODIUM STEAROYL GLUTAMATE; GLYCERYL STEARATE SE; COCO-CAPRYLATE; ALMOND OIL; SUNFLOWER OIL; SHEA BUTTER; XANTHAN GUM; CALENDULA ARVENSIS LEAF; .ALPHA.-TOCOPHEROL ACETATE, D-; GLYCERYL CAPRYLATE; SODIUM LEVULINATE

ACTIVE INGREDIENT

Zinc Oxide 12%

PURPOSE

Skin Protectant

Keep out of reach of children

Uses and Indications

For the relief of diaper rash, minor cuts and burns

Directions

Apply cream, liberally, and as often as necessary to dry skin, with each diaper change, especially at bedtime or anytime when exposure to wet diapers may be prolonged.

Warnings

For external use only

Avoider contact with eyes. If any adverse reaction develops, stop use, and contact a physician.

Questions

www.itchy.net.au

Made in Australia

Grahams Natural Alternatives Pty Ltd

7 Palings Crt, Nerang, QLD 4211 Australia

Inactive Ingredients

Purified Water, Betaine,
Glycerin, Cetearyl Alcohol, Glyceryl Stearate SE, Coco-
Caprylate, Prunus Amygdalus Dulcis (Sweet Almond) Oil),
Helianthus Annuus (Sunflower) Seed Oil, Butyrospermum
Parkii (Shea Butter), Beeswax, Caprylic/Capric
Triglyceride, Sodium Stearoyl Glutamate, Jojoba Oil,
Xanthan Gum, Chamomile Extract, Calendula Extract,
Tocopherol Acetate, Phenoxyethanol, Capryl Glycol